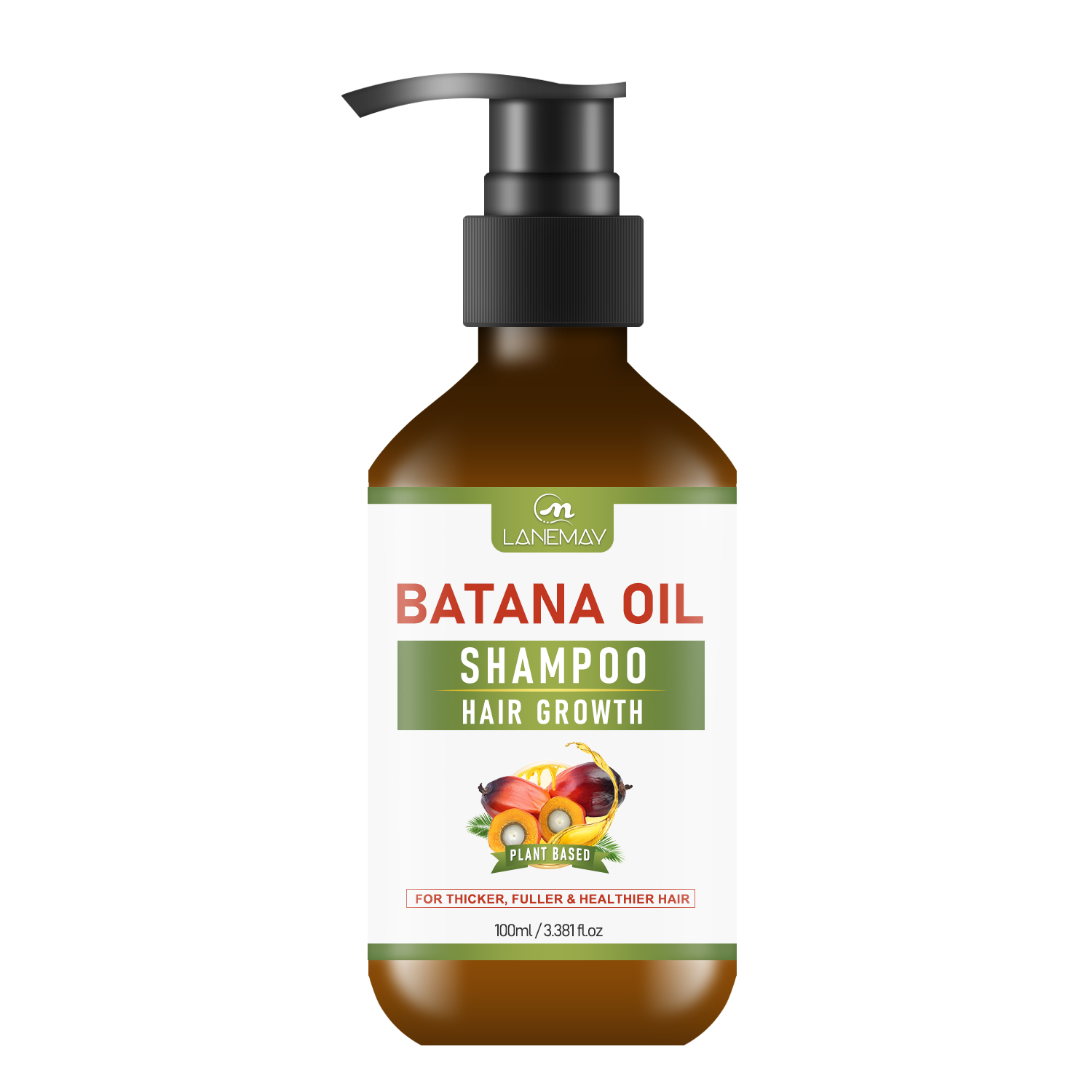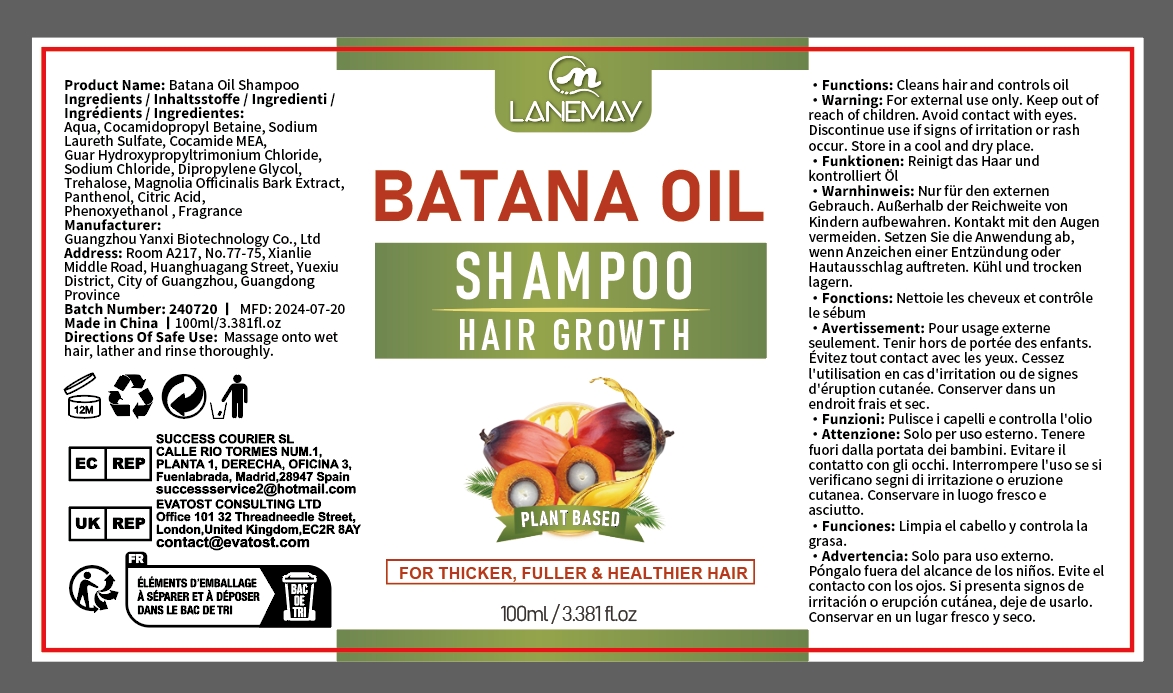 DRUG LABEL: Batana OilShampoo
NDC: 84025-113 | Form: SHAMPOO
Manufacturer: Guangzhou Yanxi Biotechnology Co.. Ltd
Category: otc | Type: HUMAN OTC DRUG LABEL
Date: 20240803

ACTIVE INGREDIENTS: DIPROPYLENE GLYCOL 3 mg/100 mL; COCAMIDOPROPYL BETAINE 5 mg/100 mL
INACTIVE INGREDIENTS: WATER

DOSAGE AND ADMINISTRATION

Shampoo for nourishing the scalp and smoothing the hair

WARNINGS

keep out of children

INACTIVE INGREDIENT

Aqua

INDICATIONS AND USAGE

For the repair and care of hair and scalp

keep out of children

PURPOSE

Nourishes the scalp, softens and smoothes hair